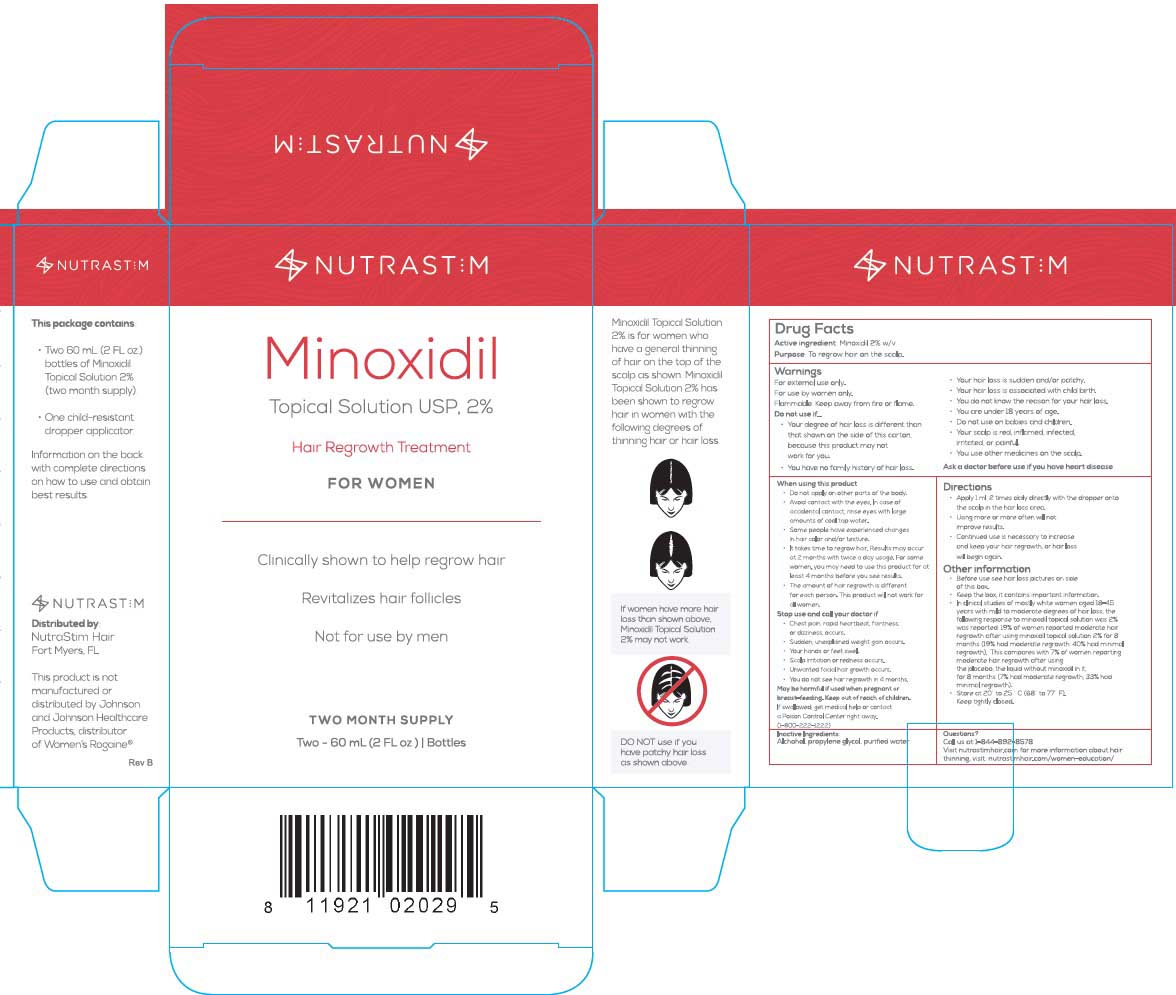 DRUG LABEL: minoxidil solution
NDC: 71517-001 | Form: SOLUTION
Manufacturer: Nutrastim Hair LLC
Category: otc | Type: HUMAN OTC DRUG LABEL
Date: 20191102

ACTIVE INGREDIENTS: MINOXIDIL 20 g/1 mL
INACTIVE INGREDIENTS: ALCOHOL; PROPYLENE GLYCOL; WATER

NUTRASTIM HAIR REGROWTH TREATMENT FOR WOMEN

PURPOSE

To regrow hair on the scalp.

WARNINGS

- For external use only.
- For use by women only.
- Flammable. Keep away from fire or flame.

DO NOT USE

- Your degree of hair loss is different than that shown on the side of this carton, because this product may not work for you.
- You have no family history of hair loss.
- Your hair loss is sudden and/or patchy.
- Your hair loss is associated with child birth.
- You do not know the reason for your hair loss.
- You are under 18 years of age.
- Do not use on babies and children.
- Your scalp is red, inflamed, infected, irritated, or painful.
- You use other medicines on the scalp.

Ask a doctor before use if you have heart disease

WHEN USING

- Do not apply on other parts of the body.
- Avoid contact with the eyes. In case of accidental contact, rinse eyes with large amounts of cool tap water.
- Some people have experienced changes in hair color and/or texture.
- It takes time to regrow hair. Results may occur at 2 months with twice a day usage. For some women, you may need to use this product for at least 4 months before you see results.
- The amount of hair regrowth is different with each person. This product will not work for all women.

STOP USE

- Chest pain, rapid heartbeat, faintness, or dizziness occurs.
- Sudden, unexplained weight gain occurs.
- Your hands or feet swell.
- Scalp irritation or redness occurs.
- Unwanted facial hair growth occurs.
- You do not see hair regrowth in 4 months.

PREGNANCY OR BREAST FEEDING

May be harmful if used when pregnant or breast-feeding.

Keep out of reach of children. If swallowed, get medical help or contact a Poison Control Center right away. (1-800-222-1222).

Directions

- Apply 1 ml, 2 times daily directly with the dropper onto the scalp in the hair loss area.
- Using more or more often will not improve results.
- Continued use is necessary to increase and keep your hair regrowth, or hair loss will begin again.

Other information

- Before use see hair loss pictures on side of this box.
- Keep the box, it contains important information.
- In clinical studies of mostly white women aged 18-45 years with mild to moderate degrees of hair loss, the following response to minoxidil topical solution was 2% was reported: 19% of women reported moderate hair regrowth after using minoxidil topical solution 2% for 8 months (19% had moderate regrowth: 40% had minimal regrowth). This compares with 7% of women reporting moderate hair regrowth after using the placebo, the liquid without minoxidil in it, for 8 months (7% had moderate regrowth; 33% had minimal regrowth).
- Store at 20° to 25° C (68° to 77° F).

Keep tightly closed.

INACTIVE INGREDIENT

Alcohol, propylene glycol, purified water

QUESTIONS

Call us at 1-844-892-8578

Visit nutrastimhair.com

for more information about hair thinning, visit

nutrastimhair.com/women-education/

ACTIVE INGREDIENT

Minoxidil 2% w/v